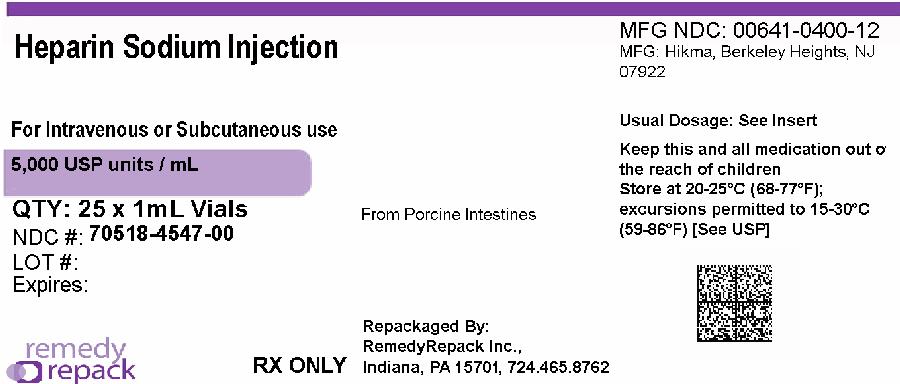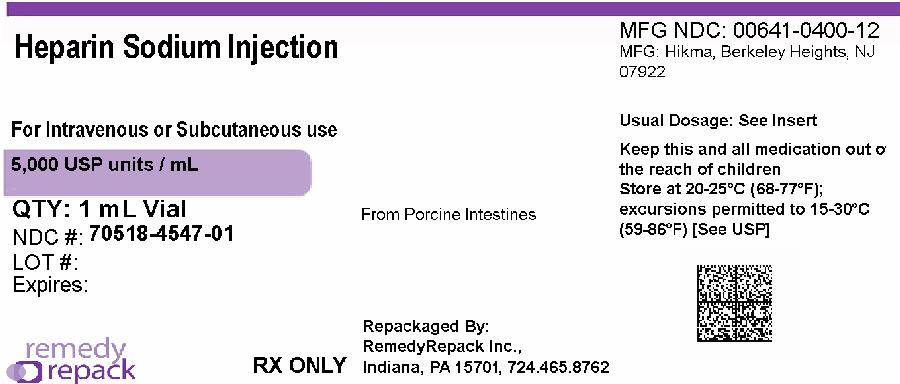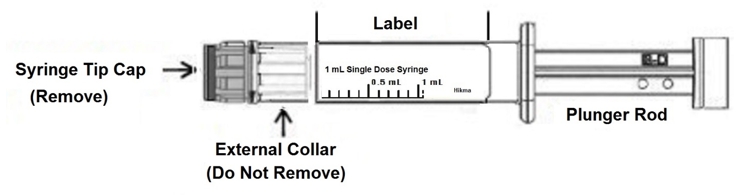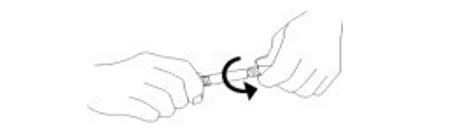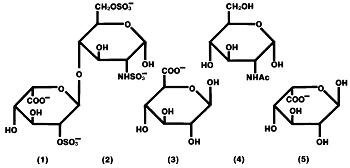 DRUG LABEL: Heparin Sodium
NDC: 70518-4547 | Form: INJECTION
Manufacturer: REMEDYREPACK INC.
Category: prescription | Type: HUMAN PRESCRIPTION DRUG LABEL
Date: 20260116

ACTIVE INGREDIENTS: HEPARIN SODIUM 5000 [USP'U]/1 mL
INACTIVE INGREDIENTS: SODIUM CHLORIDE 7 mg/1 mL; BENZYL ALCOHOL 0.01 mL/1 mL

HIGHLIGHTS OF PRESCRIBING INFORMATION

These highlights do not include all the information needed to use HEPARIN SODIUM INJECTIONsafely and effectively. See full prescribing information for HEPARIN SODIUM INJECTION.
HEPARIN SODIUM INJECTION, for intravenous or subcutaneous use
Initial U.S. Approval: 1939

1 INDICATIONS AND USAGE

HEPARIN SODIUM INJECTION is an anticoagulant indicated for (1)

- Prophylaxis and treatment of venous thrombosis and pulmonary embolism
- Prevention of postoperative deep venous thrombosis and pulmonary embolism in patients undergoing major abdominothoracic surgery or who, for other reasons, are at risk of developing thromboembolic disease
- Atrial fibrillation with embolization
- Treatment of acute and chronic consumptive coagulopathies (disseminated intravascular coagulation)
- Prevention of clotting in arterial and cardiac surgery
- Prophylaxis and treatment of peripheral arterial embolism
- Use as an anticoagulant in blood transfusions, extracorporeal circulation, and dialysis procedures

2 DOSAGE AND ADMINISTRATION

Recommended Adult Dosages:

- Therapeutic Anticoagulant Effect with Full-Dose Heparin†(2.4)

Deep Subcutaneous (Intrafat) Injection Use a different site for each injection | Initial Dose | 5,000 units by intravenous injection, followed by 10,000 to 20,000 units of a concentrated solution, subcutaneously
Deep Subcutaneous (Intrafat) Injection Use a different site for each injection | Every 8 hours or; Every 12 hours | 8,000 to 10,000 units of a concentrated solution; 15,000 to 20,000 units of a concentrated solution
Intermittent Intravenous Injection | Initial dose | 10,000 units, either undiluted or in 50 to 100 mL of 0.9% Sodium Chloride Injection, USP
Intermittent Intravenous Injection | Every 4 to 6 hours | 5,000 to 10,000 units, either undiluted or in 50 to 100 mL of 0.9% Sodium Chloride Injection, USP
Intravenous Infusion | Initial dose | 5,000 units by intravenous injection
Intravenous Infusion | Continuous | 20,000 to 40,000 units/24 hours in 1000 mL of 0.9% Sodium Chloride Injection, USP (or in any compatible solution) for infusion
†Based on 150 lb (68 kg) patient. Adjust dose based on laboratory monitoring.

3 DOSAGE FORMS AND STRENGTHS

Injection (preserved with Benzyl Alcohol)

Single-dose Vials

- 5,000 USP units per mL

4 CONTRAINDICATIONS

- Severe thrombocytopenia (4)
- When suitable blood coagulation tests, e.g., the whole blood clotting time, partial thromboplastin time, etc., cannot be performed at appropriate intervals (4)
- An uncontrolled active bleeding state, except when this is due to disseminated intravascular coagulation (4)

5 WARNINGS AND PRECAUTIONS

- Fatal Medication Errors: Confirm choice of correct strength prior to administration (5.1)
- Hemorrhage: Fatal cases have occurred. Use caution in conditions with increased risk of hemorrhage (5.2)
- HIT and HITTS: Monitor for signs and symptoms and discontinue if indicative of HIT and HITTS (5.3)
- Benzyl Alcohol Toxicity: Do not use benzyl alcohol-preserved drugs in neonates and infants. (5.4)
- Monitoring: Blood coagulation tests guide therapy for full-dose heparin.
- Monitor platelet count and hematocrit in all patients receiving heparin (5.5, 5.6)

6 ADVERSE REACTIONS

Most common adverse reactions are hemorrhage, thrombocytopenia, HIT and HITTS, injection site irritation, general hypersensitivity reactions, and elevations of aminotransferase levels. (6.1)

To report SUSPECTED ADVERSE REACTIONS, contact Hikma Pharmaceuticals USA Inc. at 1-877-845-0689 or FDA at 1-800-FDA-1088 orwww.fda.gov/medwatch.

7 DRUG INTERACTIONS

Drugs that interfere with platelet aggregation: May induce bleeding (7.2)

8 USE IN SPECIFIC POPULATIONS

- Pregnancy: Preservative-free formulation recommended. Limited human data in pregnant women. (8.1)
- Lactation: Advise females not to breastfeed. (8.2)
- Pediatric Use: Use preservative-free formulation in neonates and infants. (8.4)
- Geriatric Use: A higher incidence of bleeding reported in patients, particularly women, over 60 years of age. (8.5)

FULL PRESCRIBING INFORMATION

1 INDICATIONS AND USAGE

Heparin Sodium Injection is indicated for:

- Prophylaxis and treatment of venous thrombosis and pulmonary embolism;
- Prevention of postoperative deep venous thrombosis and pulmonary embolism in patients undergoing major abdominothoracic surgery or who, for other reasons, are at risk of developing thromboembolic disease;
- Atrial fibrillation with embolization;
- Treatment of acute and chronic consumptive coagulopathies (disseminated intravascular coagulation);
- Prevention of clotting in arterial and cardiac surgery;
- Prophylaxis and treatment of peripheral arterial embolism.
- Anticoagulant use in blood transfusions, extracorporeal circulation, and dialysis procedures.

2 DOSAGE AND ADMINISTRATION

2.1 Preparation for Administration

Confirm the choice of the correct Heparin Sodium Injection vial to ensure that the 1 mL vial is not confused with a “catheter lock flush” vial or other 1 mL vial of incorrect strength [s ee Warnings and Precautions (5.1)] .Confirm the selection of the correct formulation and strength prior to administration of the drug.

To lessen this risk, the 1 mL vial includes a red cautionary label that extends above the main label. Read the cautionary statement and confirm that you have selected the correct medication and strength. Then locate the “Tear Here” point on the label, and remove this red cautionary label prior to removing the flip-off cap.

When heparin is added to an infusion solution for continuous intravenous administration, invert the container repeatedly to ensure adequate mixing and prevent pooling of the heparin in the solution.

Inspect parenteral drug products visually for particulate matter and discoloration prior to administration, whenever solution and container permit. Use only if solution is clear and the seal is intact. Do not use if solution is discolored or contains a precipitate.

Administer Heparin Sodium Injection by intermittent intravenous injection, intravenous infusion, or deep subcutaneous (intrafat, i.e., above the iliac crest or abdominal fat layer) injection. Do not administer Heparin Sodium Injection by intramuscular injection because of the risk of hematoma at the injection site [ see Adverse Reactions (6)].

2.2 Instructions for Use of Prefilled Syringe

CAUTION: Certain glass syringes may malfunction, break or clog when connected to some Needleless Luer Access Devices (NLADs) and needles. This syringe has a larger internal syringe tip and an external collar (luer collar). The external collar must remain attached to the syringe. Data show that the syringe achieves acceptable connections with the BD Eclipse™ Needle and the Terumo SurGuard2™ Safety Needle and with the following non-center post NLADs: Alaris SMARTSITE™, B-Braun ULTRASITE™, BD-Q SYTE™, Maximum MAX PLUS™, and B-Braun SAFSITE™. The data also show acceptable connections are achieved to the center post ICU Medical CLAVE™. However, spontaneous disconnection of this glass syringe from needles and NLADs with leakage of drug product may occur. Assure that the needle or NLAD is securely attached before beginning the injection. Visually inspect the glass syringe-needle or glass syringe-NLAD connection before and during drug administration. Refer to Figure 1 for syringe diagram.

Figure 1

1. Inspect the outer packaging (plastic tube) by verifying:

- plastic tube integrity

- drug name

- drug strength

- dose volume

- route of administration

- expiration date to be sure that the drug has not expired

- sterile field applicability

Do not use if package has been damaged.

2. Remove the plastic tube cap of the outer packaging to access the syringe.

3. Remove the syringe from the plastic tube.

4. Perform visual inspection on the syringe by verifying:

- absence of syringe damage

- absence of external particles

- absence of internal particles

- proper drug color

- expiration date to be sure that the drug has not expired

- drug name

- drug strength

- dose volume

- route of administration

- sterile field applicability

5. Push plunger rod slightly to break the stopper loose while tip cap is still on.

6. Remove tip cap by twisting it off. (See Figure 2)

Figure 2

7. Discard the tip cap.

8. Expel air bubble.

9. Adjust dose by expelling extra volume (where applicable) from the syringe into sterile material prior to administration.

10. Connect the syringe to appropriate injection connection depending on route of administration. Before injection, ensure that the syringe is securely attached to the needle or needleless luer access device (NLAD).

11. Depress plunger rod to deliver medication. Ensure that pressure is maintained on the plunger rod during the entire administration.

12. Remove syringe from NLAD (if applicable) and discard into appropriate receptacle. To prevent needle-stick injuries, needles should not be recapped.

NOTES:

- All steps must be done sequentially

- Do not autoclave syringe

- Do not use this product on a sterile field

- Do not introduce any other fluid into the syringe at any time

- This product is for single dose only; discard unused portion

2.3 Laboratory Monitoring for Efficacy and Safety

Adjust the dosage of Heparin Sodium Injection according to the patient’s coagulation test results. Dosage is considered adequate when the activated partial thromboplastin time (aPTT) is 1.5 to 2 times normal or when the whole blood clotting time is elevated approximately 2.5 to 3 times the control value. When initiating treatment with Heparin Sodium Injection by continuous intravenous infusion, determine the coagulation status (aPTT, INR, platelet count) at baseline and continue to follow aPTT approximately every 4 hours and then at appropriate intervals thereafter. When the drug is administered intermittently by intravenous injection, perform coagulation tests before each injection during the initiation of treatment and at appropriate intervals thereafter. After deep subcutaneous (intrafat) injections, tests for adequacy of dosage are best performed on samples drawn 4 to 6 hours after the injection.

Periodic platelet counts and hematocrits are recommended during the entire course of heparin therapy, regardless of the route of administration.

2.4 Therapeutic Anticoagulant Effect with Full-Dose Heparin

The dosing recommendations in Table 1 are based on clinical experience. Although dosages must be adjusted for the individual patient according to the results of suitable laboratory tests, the following dosage schedules may be used as guidelines:

Table 1: Recommended Adult Full-Dose Heparin Regimens for Therapeutic Anticoagulant Effect

METHOD OF ADMINISTRATION | FREQUENCY | RECOMMENDED DOSE [based on 150 lb (68 kg) patient]
Deep Subcutaneous (Intrafat) Injection | Initial dose | 5,000 units by intravenous injection, followed by 10,000 to 20,000 units of a concentrated solution, subcutaneously
A different site should be used for each injection to prevent the development of massive hematoma | Every 8 hours or | 8,000 to 10,000 units of a concentrated solution
A different site should be used for each injection to prevent the development of massive hematoma | Every 12 hours | 15,000 to 20,000 units of a concentrated solution
Intermittent Intravenous Injection | Initial dose | 10,000 units, either undiluted or in 50 to 100 mL of 0.9% Sodium Chloride Injection, USP
Intermittent Intravenous Injection | Every 4 to 6 hours | 5,000 to 10,000 units, either undiluted or in 50 to 100 mL of 0.9% Sodium Chloride Injection, USP
Intravenous Infusion | Initial dose | 5,000 units by intravenous injection
Intravenous Infusion | Continuous | 20,000 to 40,000 units/24 hours in 1000 mL of 0.9% Sodium Chloride Injection, USP (or in any compatible solution) for infusion

2.5 Pediatric Use

Do not use benzyl alcohol-preserved drugs in neonates and infants. Use preservative-free Heparin Sodium Injection in neonates and infants [ see Warnings and Precautions (5.4)].

There are no adequate and well controlled studies on heparin use in pediatric patients. Pediatric dosing recommendations are based on clinical experience. In general, the following dosage schedule may be used as a guideline in pediatric patients:

Initial Dose | 75 to 100 units/kg (Intravenous bolus over 10 minutes)
Maintenance Dose | Infants: 25 to 30 units/kg/hour; Infants < 2 months have the highest requirements (average 28 units/kg/hour); Children > 1 year of age: 18 to 20 units/kg/hour; Older children may require less heparin, similar to weight-adjusted adult dosage
Monitoring | Adjust heparin to maintain APTT of 60 to 85 seconds, assuming this reflects an anti-Factor Xa level of 0.35 to 0.70

2.6 Cardiovascular Surgery

Patients undergoing total body perfusion for open-heart surgery should receive an initial dose of not less than 150 units of heparin sodium per kilogram of body weight. Frequently, a dose of 300 units per kilogram is used for procedures estimated to last less than 60 minutes, or 400 units per kilogram for those estimated to last longer than 60 minutes.

2.7 Low-Dose Prophylaxis of Postoperative Thromboembolism

The most widely used dosage has been 5,000 units 2 hours before surgery and 5,000 units every 8 to 12 hours thereafter for 7 days or until the patient is fully ambulatory, whichever is longer. Administer the heparin by deep subcutaneous (intrafat, i.e., above the iliac crest or abdominal fat layer, arm, or thigh) injection with a fine (25- to 26-gauge) needle to minimize tissue trauma.

2.8 Blood Transfusion

Add 450 USP units to 600 USP units of heparin sodium per 100 mL of whole blood to prevent coagulation. Usually, 7,500 USP units of heparin sodium are added to 100 mL of 0.9% Sodium Chloride Injection, USP (or 75,000 USP units per 1000 mL of 0.9% Sodium Chloride Injection, USP) and mixed; from this sterile solution, 6 mL to 8 mL are added per 100 mL of whole blood.

2.9 Converting to Warfarin

To ensure continuous anticoagulation when converting from Heparin Sodium Injection to warfarin, continue full heparin therapy for several days until the INR (prothrombin time) has reached a stable therapeutic range. Heparin therapy may then be discontinued without tapering [see Drug Interactions (7.1)] .

2.10 Converting to Oral Anticoagulants other than Warfarin

For patients currently receiving intravenous heparin, stop intravenous infusion of heparin sodium immediately after administering the first dose of oral anticoagulant; or for intermittent intravenous administration of heparin sodium, start oral anticoagulant 0 to 2 hours before the time that the next dose of heparin was to have been administered.

2.11 Extracorporeal Dialysis

Follow equipment manufacturers’ operating directions carefully. A dose of 25 units/kg to 30 units/kg followed by an infusion rate of 1,500 units/hour to 2,000 units/hour is suggested based on pharmacodynamic data if specific manufacturers’ recommendations are not available.

3 DOSAGE FORMS AND STRENGTHS

Heparin Sodium Injection, USP preserved with benzyl alcohol is available as follows:

- 5,000 USP units/mL single-dose vials

4 CONTRAINDICATIONS

The use of Heparin Sodium Injection is contraindicated in patients with the following conditions:

- History of heparin-induced thrombocytopenia and heparin-induced thrombocytopenia and thrombosis [see Warnings and Precautions (5.3)] ;
- Known hypersensitivity to heparin or pork products (e.g., anaphylactoid reactions) [see Adverse Reactions (6.1)] ;
- In whom suitable blood coagulation tests, e.g., the whole blood clotting time, partial thromboplastin time, etc., cannot be performed at appropriate intervals (this contraindication refers to full-dose heparin; there is usually no need to monitor coagulation parameters in patients receiving low-dose heparin);
- An uncontrolled active bleeding state [ see Warnings and Precautions (5.2)], except when this is due to disseminated intravascular coagulation.

5 WARNINGS AND PRECAUTIONS

5.1 Fatal Medication Errors

Do not use Heparin Sodium Injection as a “catheter lock flush” product. Heparin Sodium Injection is supplied in vials and syringes containing various strengths of heparin, including vials that contain a highly concentrated solution of 10,000 units in 1 mL. Fatal hemorrhages have occurred in pediatric patients due to medication errors in which 1 mL Heparin Sodium Injection vials were confused with 1 mL “catheter lock flush” vials. Carefully examine all Heparin Sodium Injection vials and syringes to confirm the correct vial or syringe choice prior to administration of the drug.

5.2 Hemorrhage

Avoid using heparin in the presence of major bleeding, except when the benefits of heparin therapy outweigh the potential risks.

Hemorrhage can occur at virtually any site in patients receiving heparin. Fatal hemorrhages have occurred. Adrenal hemorrhage (with resultant acute adrenal insufficiency), ovarian hemorrhage, and retroperitoneal hemorrhage have occurred during anticoagulant therapy with heparin [see Adverse Reactions (6.1)] . A higher incidence of bleeding has been reported in patients, particularly women, over 60 years of age [see Clinical Pharmacology (12.3)] . An unexplained fall in hematocrit, fall in blood pressure or any other unexplained symptom should lead to serious consideration of a hemorrhagic event.

Use heparin sodium with caution in disease states in which there is increased risk of hemorrhage, including:

- Cardiovascular - Subacute bacterial endocarditis, severe hypertension.
- Surgical - During and immediately following (a) spinal tap or spinal anesthesia or (b) major surgery, especially involving the brain, spinal cord, or eye.
- Hematologic - Conditions associated with increased bleeding tendencies, such as hemophilia, thrombocytopenia and some vascular purpuras.
- Patients with hereditary antithrombin III deficiency receiving concurrent antithrombin III therapy - The anticoagulant effect of heparin is enhanced by concurrent treatment with antithrombin III (human) in patients with hereditary antithrombin III deficiency. To reduce the risk of bleeding, reduce the heparin dose during concomitant treatment with antithrombin III (human).
- Gastrointestinal - Ulcerative lesions and continuous tube drainage of the stomach or small intestine.
- Other - Menstruation, liver disease with impaired hemostasis.

5.3 Heparin-Induced Thrombocytopenia and Heparin-Induced Thrombocytopenia and Thrombosis

Heparin-induced thrombocytopenia (HIT) is a serious antibody-mediated reaction. HIT occurs in patients treated with heparin and is due to the development of antibodies to a platelet Factor 4-heparin complex that induce in vivoplatelet aggregation. HIT may progress to the development of venous and arterial thromboses, a condition referred to as heparin-induced thrombocytopenia with thrombosis (HITT). Thrombotic events may also be the initial presentation for HITT. These serious thromboembolic events include deep vein thrombosis, pulmonary embolism, cerebral vein thrombosis, limb ischemia, stroke, myocardial infarction, mesenteric thrombosis, renal arterial thrombosis, skin necrosis, gangrene of the extremities that may lead to amputation, and possibly death. If the platelet count falls below 100,000/mm^3or if recurrent thrombosis develops, promptly discontinue heparin, evaluate for HIT and HITT, and, if necessary, administer an alternative anticoagulant.

HIT or HITT can occur up to several weeks after the discontinuation of heparin therapy. Patients presenting with thrombocytopenia or thrombosis after discontinuation of heparin sodium should be evaluated for HIT or HITT.

5.4 Risk of Serious Adverse Reactions in Infants Due to Benzyl Alcohol Preservative

Serious and fatal adverse reactions including “gasping syndrome” can occur in neonates and infants treated with benzyl alcohol-preserved drugs, including Heparin Sodium Injection vials. The “gasping syndrome” is characterized by central nervous system depression, metabolic acidosis, and gasping respirations.

When prescribing Heparin Sodium Injection vials in infants consider the combined daily metabolic load of benzyl alcohol from all sources including Heparin Sodium Injection vials (contains 10.42 mg of benzyl alcohol per mL) and other drugs containing benzyl alcohol. The minimum amount of benzyl alcohol at which toxicity may occur is not known [see Use in Specific Populations (8.4)] .

5.5 Thrombocytopenia

Thrombocytopenia in patients receiving heparin has been reported at frequencies up to 30%. It can occur 2 to 20 days (average 5 to 9) following the onset of heparin therapy. Obtain platelet counts before and periodically during heparin therapy. Monitor thrombocytopenia of any degree closely. If the count falls below 100,000/mm^3or if recurrent thrombosis develops, promptly discontinue heparin, evaluate for HIT and HITT, and, if necessary, administer an alternative anticoagulant [see Warnings and Precautions (5.3)].

5.6 Coagulation Testing and Monitoring

When using a full dose heparin regimen, adjust the heparin dose based on frequent blood coagulation tests. If the coagulation test is unduly prolonged or if hemorrhage occurs, discontinue heparin promptly [ see Overdosage (10)]. Periodic platelet counts and hematocrits are recommended during the entire course of heparin therapy, regardless of the route of administration [ see Dosage and Administration (2.3)].

5.7 Heparin Resistance

Resistance to heparin is frequently encountered in fever, thrombosis, thrombophlebitis, infections with thrombosing tendencies, myocardial infarction, cancer, in postsurgical patients, and patients with antithrombin III deficiency. Close monitoring of coagulation tests is recommended in these cases. Adjustment of heparin doses based on anti-Factor Xa levels may be warranted.

5.8 Hypersensitivity

Patients with documented hypersensitivity to heparin should be given the drug only in clearly life-threatening situations.

Because Heparin Sodium Injection is derived from animal tissue, it should be used with caution in patients with a history of allergy.

6 ADVERSE REACTIONS

The following clinically significant adverse reactions are described elsewhere in the labeling:

- Hemorrhage [ see Warnings and Precautions (5.2)]
- Heparin-Induced Thrombocytopenia and Heparin-Induced Thrombocytopenia and Thrombosis [ see Warnings and Precautions (5.3)]
- Risk of Serious Adverse Reactions in Infants Due to Benzyl Alcohol Preservative [ see Warnings and Precautions (5.4)]
- Thrombocytopenia [ see Warnings and Precautions (5.5)]
- Heparin Resistance [ see Warnings and Precautions (5.7)]
- Hypersensitivity [ see Warnings and Precautions (5.8)]

6.1 Postmarketing Experience

The following adverse reactions have been identified during post approval use of Heparin Sodium Injection. Because these reactions are reported voluntarily from a population of uncertain size, it is not always possible to reliably estimate their frequency or establish a causal relationship to drug exposure.

- Hemorrhage is the chief complication that may result from heparin therapy [ see Warnings and Precautions (5.2)]. Gastrointestinal or urinary tract bleeding during anticoagulant therapy may indicate the presence of an underlying occult lesion.Bleeding can occur at any site but certain specific hemorrhagic complications may be difficult to detect:
  - Adrenal hemorrhage, with resultant acute adrenal insufficiency, has occurred with heparin therapy, including fatal cases.
  - Ovarian (corpus luteum) hemorrhage developed in a number of women of reproductive age receiving short- or long-term heparin therapy.
  - Retroperitoneal hemorrhage
- HIT and HITT, including delayed onset cases [ see Warnings and Precautions (5.3)].
- Local Irritation –Local irritation, erythema, mild pain, hematoma or ulceration may follow deep subcutaneous (intrafat) injection of heparin sodium. Because these complications are much more common after intramuscular use, the intramuscular route is not recommended.
- Histamine-like reactions – Such reactions have been observed at the site of injections. Necrosis of the skin has been reported at the site of subcutaneous injection of heparin, occasionally requiring skin grafting [ see Warnings and Precautions (5.3)].
- Hypersensitivity –Generalized hypersensitivity reactions have been reported, with chills, fever and urticaria as the most usual manifestations, and asthma, rhinitis, lacrimation, headache, nausea and vomiting, and anaphylactoid reactions, including shock, occurring less frequently. Itching and burning, especially on the plantar side of the feet, may occur [ see Warnings and Precautions (5.8)].
- Elevations of aminotransferases – Significant elevations of aspartate aminotransferase (AST) and alanine aminotransferase (ALT) levels have occurred in patients who have received heparin.
- Miscellaneous -Osteoporosis following long-term administration of high doses of heparin, cutaneous necrosis after systemic administration, suppression of aldosterone synthesis, delayed transient alopecia, priapism, and rebound hyperlipemia on discontinuation of heparin sodium have also been reported.

7 DRUG INTERACTIONS

7.1 Oral Anticoagulants

Heparin sodium may prolong the one-stage prothrombin time. Therefore, when heparin sodium is given with dicumarol or warfarin sodium, a period of at least 5 hours after the last intravenous dose or 24 hours after the last subcutaneous dose should elapse before blood is drawn, if a valid prothrombin time is to be obtained.

7.2 Platelet Inhibitors

Drugs such as NSAIDS (including salicylic acid, ibuprofen, indomethacin, and celecoxib), dextran, phenylbutazone, thienopyridines, dipyridamole, hydroxychloroquine, glycoprotein IIb/IIIa antagonists (including abciximab, eptifibatide, and tirofiban), and others that interfere with platelet-aggregation reactions (the main hemostatic defense of heparinized patients) may induce bleeding and should be used with caution in patients receiving heparin sodium. To reduce the risk of bleeding, a reduction in the dose of antiplatelet agent or heparin is recommended.

7.3 Other Interactions

Digitalis, tetracyclines, nicotine or antihistamines may partially counteract the anticoagulant action of heparin sodium. Intravenous nitroglycerin administered to heparinized patients may result in a decrease of the partial thromboplastin time with subsequent rebound effect upon discontinuation of nitroglycerin. Careful monitoring of partial thromboplastin time and adjustment of heparin dosage are recommended during coadministration of heparin and intravenous nitroglycerin.

Antithrombin III (human) – The anticoagulant effect of heparin is enhanced by concurrent treatment with antithrombin III (human) in patients with hereditary antithrombin III deficiency. To reduce the risk of bleeding, a reduced dosage of heparin is recommended during treatment with antithrombin III (human).

8 USE IN SPECIFIC POPULATIONS

8.1 Pregnancy

Risk Summary

There are no available data on Heparin Sodium Injection use in pregnant women to inform a drug-associated risk of major birth defects and miscarriage. In published reports, heparin exposure during pregnancy did not show evidence of an increased risk of adverse maternal or fetal outcomes in humans. No teratogenicity, but early embryo-fetal death was observed in animal reproduction studies with administration of heparin sodium to pregnant rats and rabbits during organogenesis at doses approximately 10 times the maximum recommended human dose (MRHD) of 45,000 units/day [ see Data]. Consider the benefits and risks of Heparin Sodium Injection for the mother and possible risks to the fetus when prescribing Heparin Sodium Injection to a pregnant woman.

If available, preservative-free Heparin Sodium Injection is recommended when heparin therapy is needed during pregnancy. There are no known adverse outcomes associated with fetal exposure to the preservative benzyl alcohol through maternal drug administration; however, the preservative benzyl alcohol can cause serious adverse events and death when administered intravenously to neonates and infants [ see Warnings and Precautions (5.4)]

The background risk of major birth defects and miscarriage for the indicated population is unknown. In the U.S. general population, the estimated background risk of major birth defects and miscarriage in clinically recognized pregnancies is 2-4% and 15-20%, respectively.

Data

Human Data

The maternal and fetal outcomes associated with uses of heparin via various dosing methods and administration routes during pregnancy have been investigated in numerous studies. These studies generally reported normal deliveries with no maternal or fetal bleeding and no other complications.

Animal Data

In a published study conducted in rats and rabbits, pregnant animals received heparin intravenously during organogenesis at a dose of 10,000 units/kg/day, approximately 10 times the maximum human daily dose based on body weight. The number of early resorptions increased in both species. There was no evidence of teratogenic effects.

8.2 Lactation

Risk Summary

If available, preservative-free Heparin Sodium Injection is recommended when heparin therapy is needed during lactation. Benzyl alcohol present in maternal serum is likely to cross into human milk and may be orally absorbed by a nursing infant. There is no information regarding the presence of Heparin Sodium Injection in human milk, the effects on the breastfed infant, or the effects on milk production. Due to its large molecular weight, heparin is not likely to be excreted in human milk, and any heparin in milk would not be orally absorbed by a nursing infant. The developmental and health benefits of breastfeeding should be considered along with the mother's clinical need for Heparin Sodium Injection and any potential adverse effects on the breastfed infant from Heparin Sodium Injection or from the underlying maternal condition [ see Use in Specific Populations (8.4)].

8.4 Pediatric Use

There are no adequate and well controlled studies on heparin use in pediatric patients. Pediatric dosing recommendations are based on clinical experience [ see Dosage and Administration (2.5)].

Carefully examine all Heparin Sodium Injection vials and syringes to confirm choice of the correct strength prior to administration of the drug. Pediatric patients, including neonates, have died as a result of medication errors in which Heparin Sodium Injection vials have been confused with “catheter lock flush” vials [ see Warnings and Precautions (5.1)].

Benzyl Alcohol Toxicity

Use preservative-free Heparin Sodium Injection in neonates and infants.

Serious adverse reactions including fatal reactions and the “gasping syndrome” occurred in premature neonates and infants in the neonatal intensive care unit who received drugs containing benzyl alcohol as a preservative. In these cases, benzyl alcohol dosages of 99 to 234 mg/kg/day produced high levels of benzyl alcohol and its metabolites in the blood and urine (blood levels of benzyl alcohol were 0.61 to 1.378 mmol/L). Additional adverse reactions included gradual neurological deterioration, seizures, intracranial hemorrhage, hematologic abnormalities, skin breakdown, hepatic and renal failure, hypotension, bradycardia, and cardiovascular collapse. Preterm, low-birth weight infants may be more likely to develop these reactions because they may be less able to metabolize benzyl alcohol.

8.5 Geriatric Use

There are limited adequate and well-controlled studies in patients 65 years and older, however, a higher incidence of bleeding has been reported in patients, particularly women, over 60 years of age [ see Warnings and Precautions (5.2)]. Patients over 60 years of age may require lower doses of heparin.

Lower doses of heparin may be indicated in these patients [ see Clinical Pharmacology (12.3)].

10 OVERDOSAGE

Bleeding is the chief sign of heparin overdosage.

Neutralization of Heparin Effect

When clinical circumstances (bleeding) require reversal of the heparin effect, protamine sulfate (1% solution) by slow infusion will neutralize heparin sodium. No more than 50 mgshould be administered, very slowly, in any 10-minute period. Each mg of protamine sulfate neutralizes approximately 100 USP heparin units. The amount of protamine required decreases over time as heparin is metabolized. Although the metabolism of heparin is complex, it may, for the purpose of choosing a protamine dose, be assumed to have a half-life of about 1/2 hour after intravenous injection.

Because fatal reactions often resembling anaphylaxis have been reported with protamine, it should be given only when resuscitation techniques and treatment of anaphylactoid shock are readily available.

For additional information consult the labeling of Protamine Sulfate Injection.

11 DESCRIPTION

Heparin is a heterogeneous group of straight-chain anionic mucopolysaccharides, called glycosaminoglycans, possessing anticoagulant properties. It is composed of polymers of alternating derivations of α-D-glucosamido (N-sulfated O-sulfated or N-acetylated) and O-sulfated uronic acid (α-L-iduronic acid or β-D-glucoronic acid).

Structure of heparin sodium (representative subunits):

Heparin Sodium Injection, USP is a sterile solution of heparin sodium derived from porcine intestinal mucosa, standardized for anticoagulant activity. It is to be administered by intravenous or deep subcutaneous routes. The potency is determined by a biological assay using a USP reference standard based on units of heparin activity per milligram.

Heparin Sodium Injection, USP preserved with Benzyl Alcohol is available in the following concentrations/mL:

Heparin Sodium | Sodium Chloride | Benzyl Alcohol
1,000 USP units | 8.6 mg | 10.42 mg
5,000 USP units | 7 mg | 10.42 mg
10,000 USP units | 5 mg | 10.42 mg

pH 5.0-7.5; sodium hydroxide and/or hydrochloric acid added, if needed, for pH adjustment.

Heparin Sodium Injection, USP, preservative-freeis available in the following concentrations:

Heparin Sodium | Sodium Chloride
5,000 USP units/1 mL | 7 mg
5,000 USP units/0.5 mL | 5 mg

pH 5.0-7.5; sodium hydroxide and/or hydrochloric acid added, if needed, for pH adjustment.

12 CLINICAL PHARMACOLOGY

12.1 Mechanism of Action

Heparin interacts with the naturally occurring plasma protein, Antithrombin III, to induce a conformational change, which markedly enhances the serine protease activity of Antithrombin III, thereby inhibiting the activated coagulation factors involved in the clotting sequence, particularly Xa and IIa. Small amounts of heparin inhibit Factor Xa, and larger amounts inhibit thrombin (Factor IIa). Heparin also prevents the formation of a stable fibrin clot by inhibiting the activation of the fibrin stabilizing factor. Heparin does not have fibrinolytic activity; therefore, it will not lyse existing clots.

12.2 Pharmacodynamics

Various times (activated clotting time, activated partial thromboplastin time, prothrombin time, whole blood clotting time) are prolonged by full therapeutic doses of heparin; in most cases, they are not measurably affected by low doses of heparin. The bleeding time is usually unaffected by heparin.

12.3 Pharmacokinetics

Absorption

Heparin is not absorbed through the gastrointestinal tract and therefore administered via parenteral route. Peak plasma concentration and the onset of action are achieved immediately after intravenous administration.

Distribution

Heparin is highly bound to antithrombin, fibrinogens, globulins, serum proteases and lipoproteins. The volume of distribution is 0.07 L/kg.

Elimination

Metabolism

Heparin does not undergo enzymatic degradation.

Excretion

Heparin is mainly cleared from the circulation by liver and reticuloendothelial cells mediated uptake into extravascular space. Heparin undergoes biphasic clearance, a) rapid saturable clearance (zero order process due to binding to proteins, endothelial cells and macrophage) and b) slower first order elimination. The plasma half-life is dose-dependent and it ranges from 0.5 to 2 h.

Specific Populations

Geriatric patients

Patients over 60 years of age, following similar doses of heparin, may have higher plasma levels of heparin and longer activated partial thromboplastin times (APTTs) compared with patients under 60 years of age [ see Use in Specific Populations (8.5)].

13 NONCLINICAL TOXICOLOGY

13.1 Carcinogenesis, Mutagenesis, Impairment of Fertility

No long-term studies in animals have been performed to evaluate carcinogenic potential of heparin. Also, no reproduction studies in animals have been performed concerning mutagenesis or impairment of fertility.

16 HOW SUPPLIED/STORAGE AND HANDLING

Heparin Sodium Injection preserved with benzyl alcohol is available in the following strengths and package sizes in single-dose vials:

25 vials: 5,000 USP units/mL, single-dose*

*Discard unused portion

NDC: 70518-4547-00

NDC: 70518-4547-01

PACKAGING: 25 in 1 PACKAGE

PACKAGING: 1 mL VIAL, TYPE 0

Store at 20°-25°C (68°-77°F) [See USP Controlled Room Temperature].

Repackaged and Distributed By:

Remedy Repack, Inc.

625 Kolter Dr. Suite #4 Indiana, PA 1-724-465-8762

17 PATIENT COUNSELING INFORMATION

Hemorrhage
Inform patients that it may take them longer than usual to stop bleeding, that they may bruise and/or bleed more easily when they are treated with heparin, and that they should report any unusual bleeding or bruising to their physician. Hemorrhage can occur at virtually any site in patients receiving heparin. Fatal hemorrhages have occurred [ see Warnings and Precautions (5.2)].

Prior to Surgery
Advise patients to inform physicians and dentists that they are receiving heparin before any surgery is scheduled [ see Warnings and Precautions (5.2)].

Heparin-Induced Thrombocytopenia
Inform patients of the risk of heparin-induced thrombocytopenia (HIT). HIT may progress to the development of venous and arterial thromboses, a condition known as heparin-induced thrombocytopenia and thrombosis (HITT). HIT and HITT can occur up to several weeks after the discontinuation of heparin therapy [ see Warnings and Precautions (5.3)].

Hypersensitivity
Inform patients that generalized hypersensitivity reactions have been reported. Necrosis of the skin has been reported at the site of subcutaneous injection of heparin [ see Warnings and Precautions (5.8), Adverse Reactions (6.1)].

Other Medications
Because of the risk of hemorrhage, advise patients to inform their physicians and dentists of all medications they are taking, including non-prescription medications, and before starting any new medication [ see Drug Interactions (7.1)].

Repackaged By / Distributed By: RemedyRepack Inc.

625 Kolter Drive, Indiana, PA 15701

(724) 465-8762

PACKAGE LABEL

DRUG: Heparin Sodium

GENERIC: Heparin Sodium

DOSAGE: INJECTION

ADMINSTRATION: INTRAVENOUS

NDC: 70518-4547-0

NDC: 70518-4547-1

PACKAGING: 1 mL in 1 VIAL

OUTER PACKAGING: 25 in 1 PACKAGE

ACTIVE INGREDIENT(S):

- HEPARIN SODIUM 5000[USP'U] in 1mL

INACTIVE INGREDIENT(S):

- SODIUM CHLORIDE
- BENZYL ALCOHOL